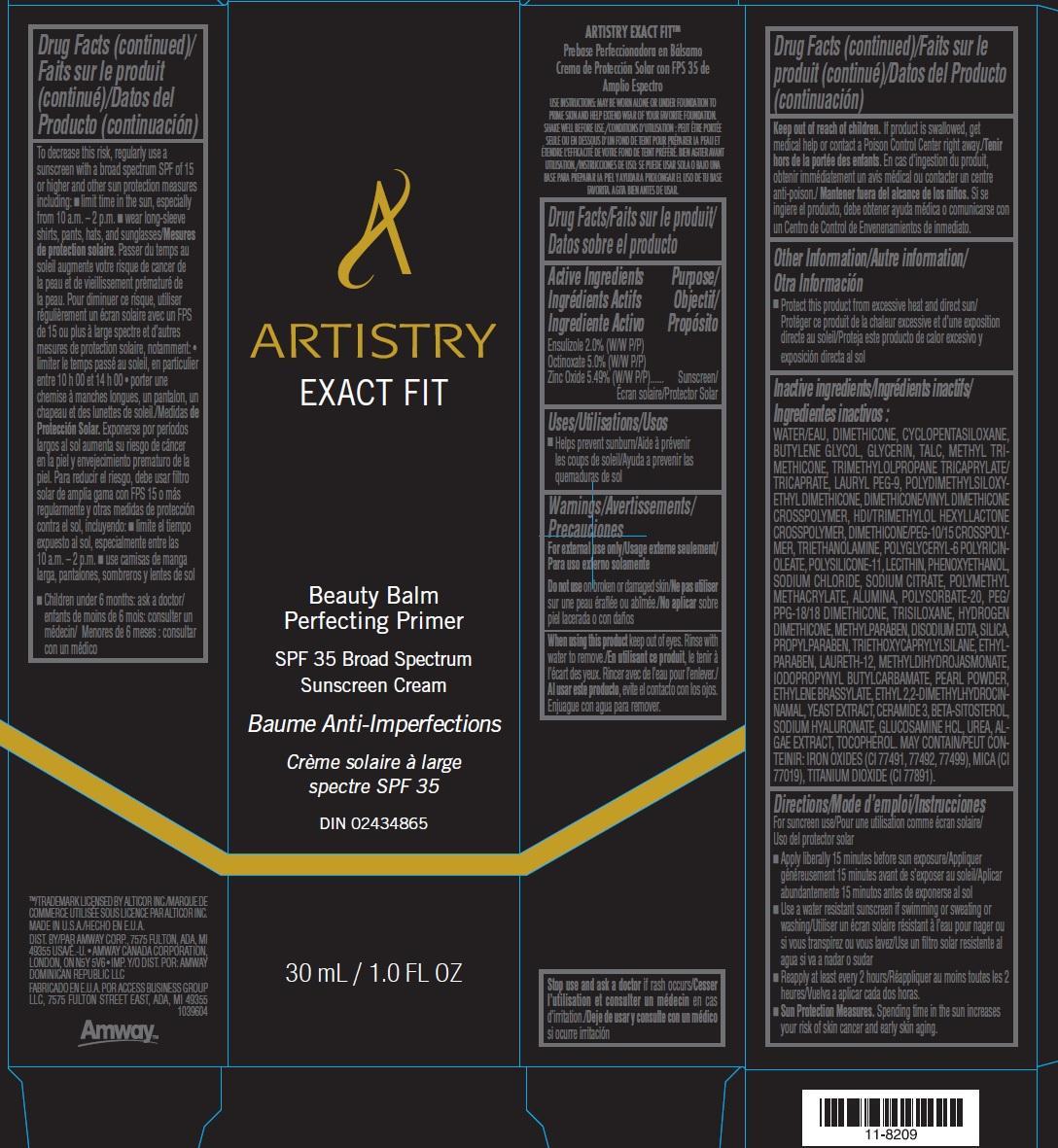 DRUG LABEL: Artistry Beauty Balm Perfecting Primer SPF 35 Broad Spectrum Sunscreen
NDC: 50390-004 | Form: CREAM
Manufacturer: Amway Corp
Category: otc | Type: HUMAN OTC DRUG LABEL
Date: 20231021

ACTIVE INGREDIENTS: ENSULIZOLE 20 mg/1 mL; OCTINOXATE 50 mg/1 mL; ZINC OXIDE 54.9 mg/1 mL
INACTIVE INGREDIENTS: WATER; DIMETHICONE; CYCLOMETHICONE 5; BUTYLENE GLYCOL; GLYCERIN; TALC; METHYL TRIMETHICONE; TRIMETHYLOLPROPANE TRICAPRYLATE/TRICAPRATE; LAURYL PEG-9 POLYDIMETHYLSILOXYETHYL DIMETHICONE; DIMETHICONE/DIENE DIMETHICONE CROSSPOLYMER; HEXAMETHYLENE DIISOCYANATE/TRIMETHYLOL HEXYLLACTONE CROSSPOLYMER; TROLAMINE; PHENOXYETHANOL; SODIUM CHLORIDE; SODIUM CITRATE; ALUMINUM OXIDE; POLYSORBATE 20; PEG/PPG-18/18 DIMETHICONE; TRISILOXANE; METHYLPARABEN; EDETATE DISODIUM; SILICON DIOXIDE; PROPYLPARABEN; TRIETHOXYCAPRYLYLSILANE; LAURETH-12; METHYL DIHYDROJASMONATE (SYNTHETIC); IODOPROPYNYL BUTYLCARBAMATE; PEARL (HYRIOPSIS CUMINGII); ETHYLENE BRASSYLATE; ETHYL 2,2-DIMETHYLHYDROCINNAMAL; YEAST, UNSPECIFIED; CERAMIDE 3; .BETA.-SITOSTEROL; HYALURONATE SODIUM; GLUCOSAMINE HYDROCHLORIDE; UREA; TOCOPHEROL; FERRIC OXIDE RED; MICA; TITANIUM DIOXIDE

Artistry Beauty Balm Perfecting Primer SPF 35 Broad Spectrum Sunscreen Cream

Active Ingredients

Ensulizole 2.0% (W/W P/P) Octinoxate 5.0% (W/W P/P) Zinc Oxide 5.49% (W/W P/P)......

Purpose

Sunscreen

Uses

■ Helps prevent sunburn

Warnings

For external use only

Do not use

on broken or damaged skin

When using this product

keep out of eyes. Rinse with water to remove.

Keep out of reach of children.

If product is swallowed, get medical help or contact a Poison Control Center right away.

Other Information

Protect this product from excessive heat and direct sun

Inactive ingredients

WATER/EAU, DIMETHICONE, CYCLOPENTASILOXANE, BUTYLENE GLYCOL, GLYCERIN, TALC, METHYL TRIMETHICONE, TRIMETHYLOLPROPANE TRICAPRYLATE/ TRICAPRATE, LAURYL PEG-9, POLYDIMETHYLSILOXYETHYL DIMETHICONE, DIMETHICONE/VINYL DIMETHICONE CROSSPOLYMER, HDI/TRIMETHYLOL HEXYLLACTONE CROSSPOLYMER, DIMETHICONE/PEG-10/15 CROSSPOLYMER, TRIETHANOLAMINE, POLYGLYCERYL-6 POLYRICINOLEATE, POLYSILICONE-11, LECITHIN, PHENOXYETHANOL, SODIUM CHLORIDE, SODIUM CITRATE, POLYMETHYL METHACRYLATE, ALUMINA, POLYSORBATE-20, PEG/ PPG-18/18 DIMETHICONE, TRISILOXANE, HYDROGEN DIMETHICONE, METHYLPARABEN, DISODIUM EDTA, SILICA, PROPYLPARABEN, TRIETHOXYCAPRYLYLSILANE, ETHYLPARABEN, LAURETH-12, METHYLDIHYDROJASMONATE, IODOPROPYNYL BUTYLCARBAMATE, PEARL POWDER,ETHYLENE BRASSYLATE, ETHYL 2,2-DIMETHYLHYDROCINNAMAL, YEAST EXTRACT, CERAMIDE 3, BETA-SITOSTEROL, SODIUM HYALURONATE, GLUCOSAMINE HCL, UREA, ALGAE EXTRACT, TOCOPHEROL. MAY CONTAIN/PEUT CONTEINIR: IRON OXIDES (CI 77491, 77492, 77499), MICA (CI 77019), TITANIUM DIOXIDE (CI 77891).

Directions

For suncreen use

- Apply liberally 15 minutes before sun exposure
- Use a water resistant sunscreen if swimming or sweating or washing
- Reapply at least every 2 hours
- Spending time in the sun increases your risk of skin cancer and early skin aging. To decrease this risk, regularly use a sunscreen with a broad spectrum SPF of 15 or higher and other sun protection measures including: ■ limit time in the sun, especially from 10 a.m. – 2 p.m. ■ wear long-sleeve shirts, pants, hats, and sunglasses Sun Protection Measures.
- Children under 6 months: ask a doctor